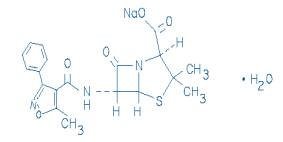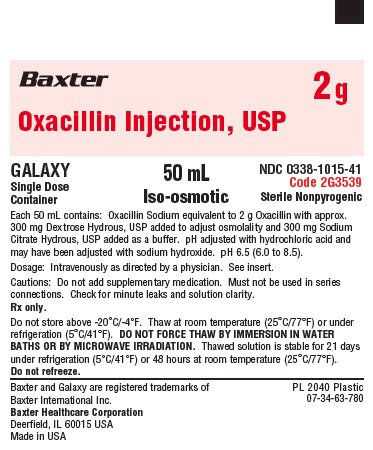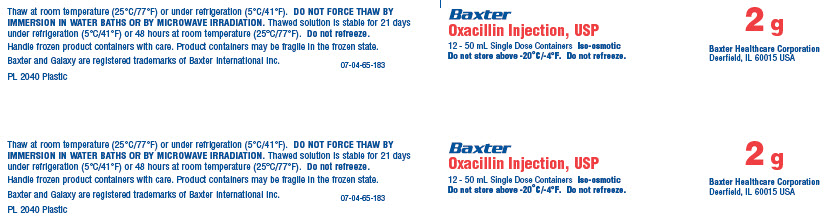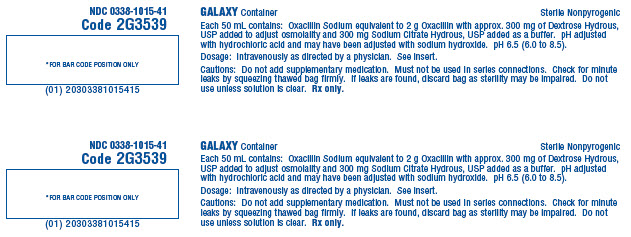 DRUG LABEL: OXACILLIN
NDC: 0338-1013 | Form: INJECTION, SOLUTION
Manufacturer: Baxter Healthcare Corporation
Category: prescription | Type: HUMAN PRESCRIPTION DRUG LABEL
Date: 20241206

ACTIVE INGREDIENTS: OXACILLIN SODIUM 1 g/50 mL
INACTIVE INGREDIENTS: DEXTROSE MONOHYDRATE 1.5 g/50 mL; TRISODIUM CITRATE DIHYDRATE 150 mg/50 mL; HYDROCHLORIC ACID; SODIUM HYDROXIDE; WATER

Oxacillin Injection, USP
in Plastic Container
For Intravenous Use Only
GALAXY Container

To reduce the development of drug-resistant bacteria and maintain the effectiveness of Oxacillin Injection, USP and other antibacterial drugs, Oxacillin Injection, USP should be used only to treat or prevent infections that are proven or strongly suspected to be caused by bacteria.

DESCRIPTION

Oxacillin Injection, USP is a sterile injectable product containing oxacillin which is added as oxacillin sodium, a semisynthetic penicillin derived from the penicillin nucleus, 6-aminopenicillanic acid. The chemical name of oxacillin sodium is 4-Thia-1-azabicyclo[3.2.0]heptane-2-carboxylic acid, 3,3-dimethyl-6-[[(5-methyl-3-phenyl-4- isoxazolyl)carbonyl]-amino]-7-oxo-, monosodium salt, monohydrate, [2S-(2α,5α,6ß)]-. It is resistant to inactivation by the enzyme penicillinase (beta-lactamase). The molecular formula of oxacillin sodium is C19H18N3NaO5S•H2O. The molecular weight is 441.44.

The structural formula of oxacillin sodium is as follows:

Oxacillin Injection, USP is a frozen, iso-osmotic, sterile, nonpyrogenic premixed 50 mL solution containing 2 g of oxacillin added as oxacillin sodium. Dextrose, USP has been added to the above dosages to adjust osmolality (approximately 300 mg as dextrose hydrous to the 2 g dosages respectively). Sodium Citrate Hydrous, USP has been added as a buffer (approximately 300 mg to the 2 g dosage). The pH has been adjusted with hydrochloric acid and may have been adjusted with sodium hydroxide. The pH is 6.5 (6.0 to 8.5). The solution is intended for intravenous use after thawing to room temperature.

This Galaxy container is fabricated from a specially designed multilayer plastic. Solutions are in contact with the polyethylene layer of this container and can leach out certain chemical components of the plastic in very small amounts within the expiration period. The suitability of the plastic has been confirmed in tests in animals according to the USP biological tests for plastic containers, as well as by tissue culture toxicity studies.

CLINICAL PHARMACOLOGY

Intravenous administration provides peak serum levels approximately 5 minutes after the injection is completed. Slow I.V. administration of 500 mg gives a peak serum level of 43 mcg/mL after 5 minutes with a half-life of 20-30 minutes.

The penicillinase-resistant penicillins bind to serum protein, mainly albumin. The degree of protein binding reported for oxacillin is 94.2% ± 2.1%. Reported values vary with the method of study and the investigator.

The penicillinase-resistant penicillins vary in the extent to which they are distributed in the body fluids. With normal doses, insignificant concentrations are found in the cerebrospinal fluid and aqueous humor. All the drugs in this class are found in therapeutic concentrations in the pleural, bile, and amniotic fluids.

The penicillinase-resistant penicillins are rapidly excreted primarily as unchanged drug in the urine by glomerular filtration and active tubular secretion. The elimination half-life for oxacillin is about 0.5 hours. Nonrenal elimination includes hepatic inactivation and excretion in bile.

Probenecid blocks the renal tubular secretion of penicillins. Therefore, the concurrent administration of probenecid prolongs the elimination of oxacillin and, consequently, increases the serum concentration.

Microbiology

Mechanism of Action

Penicillinase-resistant penicillins exert a bactericidal action against penicillin susceptible microorganisms during the state of active multiplication. All penicillins inhibit the biosynthesis of the bacterial cell wall.

Resistance

Resistance to penicillins may be mediated by destruction of the beta-lactam ring by a beta-lactamase, altered affinity of penicillin for target, or decreased penetration of the antibiotic to reach the target site.

Resistance to oxacillin (or cefoxitin) implies resistance to all other beta-lactam agents, except newer agents with activity against methicillin-resistant Staphylococcus aureus.

Susceptibility Test Methods

For specific information regarding susceptibility test interpretive criteria and associated test methods and quality control standards recognized by FDA for this drug, please see: http://www.fda.gov/STIC.

INDICATIONS AND USAGE

Oxacillin is indicated in the treatment of infections caused by penicillinase producing staphylococci which have demonstrated susceptibility to the drug. Cultures and susceptibility tests should be performed initially to determine the causative organism and its susceptibility to the drug. (See CLINICAL PHARMACOLOGY - Susceptibility Test Methods.)

Oxacillin may be used to initiate therapy in suspected cases of resistant staphylococcal infections prior to the availability of susceptibility test results. Oxacillin should not be used in infections caused by organisms susceptible to penicillin G. If the susceptibility tests indicate that the infection is due to an organism other than a resistant Staphylococcus, therapy should not be continued with oxacillin.

To reduce the development of drug-resistant bacteria and maintain the effectiveness of Oxacillin Injection, USP and other antibacterial drugs, Oxacillin Injection, USP should be used only to treat or prevent infections that are proven or strongly suspected to be caused by susceptible bacteria. When culture and susceptibility information are available, they should be considered in selecting or modifying antibacterial therapy. In the absence of such data, local epidemiology and susceptibility patterns may contribute to the empiric selection of therapy.

CONTRAINDICATIONS

A history of a hypersensitivity (anaphylactic) reaction to any penicillin is a contraindication. Solutions containing dextrose may be contraindicated in patients with known allergy to corn or corn products.

WARNINGS

Serious and occasionally fatal hypersensitivity (anaphylactic shock with collapse) reactions have occurred in patients receiving penicillin. The incidence of anaphylactic shock in all penicillin-treated patients is between 0.015 and 0.04 percent. Anaphylactic shock resulting in death has occurred in approximately 0.002 percent of the patients treated. Although anaphylaxis is more frequent following parenteral administration, it has occurred in patients receiving oral penicillins.

When penicillin therapy is indicated, it should be initiated only after a comprehensive patient drug and allergy history has been obtained. If an allergic reaction occurs, the drug should be discontinued and the patient should receive supportive treatment, e.g., artificial maintenance of ventilation, pressor amines, antihistamines, and corticosteroids. Individuals with a history of penicillin hypersensitivity may also experience allergic reactions when treated with a cephalosporin.

Clostridium difficile associated diarrhea (CDAD) has been reported with use of nearly all antibacterial agents, including Oxacillin Injection, USP, and may range in severity from mild diarrhea to fatal colitis. Treatment with antibacterial agents alters the normal flora of the colon leading to overgrowth of C. difficile.

C. difficile produces toxins A and B which contribute to the development of CDAD. Hypertoxin producing strains of C. difficile cause increased morbidity and mortality, as these infections can be refractory to antimicrobial therapy and may require colectomy. CDAD must be considered in all patients who present with diarrhea following antibiotic use. Careful medical history is necessary since CDAD has been reported to occur over two months after the administration of antibacterial agents.

If CDAD is suspected or confirmed, ongoing antibiotic use not directed against C. difficile may need to be discontinued. Appropriate fluid and electrolyte management, protein supplementation, antibiotic treatment of C. difficile, and surgical evaluation should be instituted as clinically indicated.

PRECAUTIONS

General

Oxacillin should generally not be administered to patients with a history of sensitivity to any penicillin. Penicillin should be used with caution in individuals with histories of significant allergies and/or asthma. Whenever allergic reactions occur, penicillin should be withdrawn unless, in the opinion of the physician, the condition being treated is life-threatening and amenable only to penicillin therapy. The use of antibiotics may result in overgrowth of nonsusceptible organisms. If new infections due to bacteria or fungi occur, the drug should be discontinued and appropriate measures taken.

Prescribing Oxacillin Injection, USP in the absence of a proven or strongly suspected bacterial infection or a prophylactic indication is unlikely to provide benefit to the patient and increases the risk of the development of drug-resistant bacteria.

Laboratory Tests

Bacteriologic studies to determine the causative organisms and their susceptibility to oxacillin should be performed. (See CLINICAL PHARMACOLOGY - Microbiology.) In the treatment of suspected staphylococcal infections, therapy should be changed to another active agent if culture tests fail to demonstrate the presence of staphylococci.

Periodic assessment of organ system function including renal, hepatic, and hematopoietic should be made during prolonged therapy with oxacillin.

Blood cultures, white blood cell, and differential cell counts should be obtained prior to initiation of therapy and at least weekly during therapy with oxacillin.

Periodic urinalysis, blood urea nitrogen, and creatinine determinations should be performed during therapy with oxacillin and dosage alterations should be considered if these values become elevated. If any impairment of renal function is suspected or known to exist, a reduction in the total dosage should be considered and blood levels monitored to avoid possible neurotoxic reactions.

AST (SGOT) and ALT (SGPT) values should be obtained periodically during therapy to monitor for possible liver function abnormalities.

Drug Interactions

Tetracycline, a bacteriostatic antibiotic, may antagonize the bactericidal effect of penicillin and concurrent use of these drugs should be avoided.

Oxacillin blood levels may be prolonged by concurrent administration of probenecid which blocks the renal tubular secretion of penicillins.

Carcinogenesis, Mutagenesis, Impairment of Fertility

No long-term animal studies have been conducted with these drugs. Studies on reproduction (nafcillin) in rats and rabbits reveal no fetal or maternal abnormalities before conception and continuously through weaning (one generation).

Pregnancy

Teratogenic Effects

Reproduction studies performed in the mouse, rat, and rabbit have revealed no evidence of impaired fertility or harm to the fetus due to the penicillinase-resistant penicillins. Human experience with the penicillins during pregnancy has not shown any positive evidence of adverse effects on the fetus. There are, however, no adequate or well-controlled studies in pregnant women showing conclusively that harmful effects of these drugs on the fetus can be excluded. Because animal reproduction studies are not always predictive of human response, this drug should be used during pregnancy only if clearly needed.

Nursing Mothers

Penicillins are excreted in human milk. Caution should be exercised when penicillins are administered to a nursing woman.

Pediatric Use

Because of incompletely developed renal function in pediatric patients, oxacillin may not be completely excreted, with abnormally high blood levels resulting. Frequent blood levels are advisable in this group with dosage adjustments when necessary. All pediatric patients treated with penicillins should be monitored closely for clinical and laboratory evidence of toxic or adverse effects. Safety and effectiveness in pediatric patients have not been established.

The potential for toxic effects in pediatric patients from chemicals that may leach from the single dose premixed intravenous preparation in plastic containers has not been evaluated.

Geriatric Use

Clinical studies of Oxacillin injection did not include sufficient number of subjects aged 65 and over to determine whether they respond differently from younger subjects. Other reported clinical experience has not identified differences in responses between the elderly and younger patients. In general, dose selection for an elderly patient should be cautious, usually starting at the low end of the dosing range, reflecting the greater frequency of decreased hepatic, renal, or cardiac function, and of concomitant disease or other drug therapy.

This drug is known to be substantially excreted by the kidney, and the risk of toxic reactions to this drug may be greater in patients with impaired renal function. Because elderly patients are more likely to have decreased renal function, care should be taken in dose selection, and it may be useful to monitor renal function.

Oxacillin Injection contains 92.4 mg (4.02 mEq) of sodium per gram. At the usual recommended doses, patients would receive between 92.4 and 554 mg/day (4.02 and 24.1 mEq) of sodium. The geriatric population may respond with a blunted natriuresis to salt loading. This may be clinically important with regard to such diseases as congestive heart failure.

Information for Patients

Patients should be counseled that antibacterial drugs including Oxacillin Injection, USP should only be used to treat bacterial infections. They do not treat viral infections (e.g., the common cold). When Oxacillin Injection, USP is prescribed to treat a bacterial infection, patients should be told that although it is common to feel better early in the course of therapy, the medication should be taken exactly as directed. Skipping doses or not completing the full course of therapy may (1) decrease the effectiveness of the immediate treatment and (2) increase the likelihood that bacteria will develop resistance and will not be treatable by Oxacillin Injection, USP or other antibacterial drugs in the future.

Diarrhea is a common problem caused by antibiotics which usually ends when the antibiotic is discontinued. Sometimes after starting treatment with antibiotics, patients can develop watery and bloody stools (with or without stomach cramps and fever) even as late as two or more months after having taken the last dose of the antibiotic. If this occurs, patients should contact their physician as soon as possible.

ADVERSE REACTIONS

Body as a Whole

The reported incidence of allergic reactions to penicillin ranges from 0.7 to 10 percent (see WARNINGS). Sensitization is usually the result of treatment but some individuals have had immediate reactions when first treated. In such cases, it is thought that the patients may have had prior exposure to the drug via trace amounts present in milk and vaccines.

Two types of allergic reactions to penicillins are noted clinically, immediate and delayed.

Immediate reactions usually occur within 20 minutes of administration and range in severity from urticaria and pruritus to angioneurotic edema, laryngospasm, bronchospasm, hypotension, vascular collapse and death. Such immediate anaphylactic reactions are very rare (see WARNINGS) and usually occur after parenteral therapy but have occurred in patients receiving oral therapy. Another type of immediate reaction, an accelerated reaction, may occur between 20 minutes and 48 hours after administration and may include urticaria, pruritus, and fever. Although laryngeal edema, laryngospasm, and hypotension occasionally occur, fatality is uncommon. Delayed allergic reactions to penicillin therapy usually occur after 48 hours and sometimes as late as 2 to 4 weeks after initiation of therapy. Manifestations of this type of reaction include serum sickness-like symptoms (i.e., fever, malaise, urticaria, myalgia, arthralgia, abdominal pain) and various skin rashes. Nausea, vomiting, diarrhea, stomatitis, black or hairy tongue, and other symptoms of gastrointestinal irritation may occur, especially during oral penicillin therapy.

Nervous System Reactions

Neurotoxic reactions similar to those observed with penicillin G may occur with large intravenous doses of oxacillin, especially with patients with renal insufficiency.

Urogenital Reactions

Renal tubular damage and interstitial nephritis have been associated infrequently with the administration of oxacillin. Manifestations of this reaction may include rash, fever, eosinophilia, hematuria, proteinuria, and renal insufficiency.

Gastrointestinal Reactions

Pseudomembranous colitis has been reported with the use of oxacillin. The onset of pseudomembranous colitis symptoms may occur during or after antibiotic treatment (see WARNINGS).

Metabolic Reactions

Hepatotoxicity, characterized by fever, nausea, and vomiting associated with abnormal liver function tests, mainly elevated SGOT levels, has been associated with the use of oxacillin.

OVERDOSAGE

The signs and symptoms of oxacillin overdosage are those described in the ADVERSE REACTIONS section. If signs or symptoms occur, discontinue use of the medication, treat symptomatically, and institute appropriate supportive measures.

DOSAGE AND ADMINISTRATION

Oxacillin Injection, USP supplied as a premixed frozen solution is to be administered as a continuous or intermittent intravenous infusion. The usual dose recommendation is as follows:

Adults
250-500 mg | I.V. every 4-6 hours (mild to moderate infections)
1 gram | I.V. every 4-6 hours (severe infections)

This container system may be inappropriate for the dosage requirements for children, infants and neonates. Other dosage forms may be more appropriate.

Bacteriologic studies to determine the causative organisms and their susceptibility to oxacillin should always be performed. Duration of therapy varies with the type of severity of infection as well as the overall condition of the patient; therefore, it should be determined by the clinical and bacteriological response of the patient. In severe staphylococcal infections, therapy with oxacillin should be continued for at least 14 days. Therapy should be continued for at least 48 hours after the patient has become afebrile, asymptomatic, and cultures are negative. Treatment of endocarditis and osteomyelitis may require a longer duration of therapy.

Concurrent administration of oxacillin and probenecid increases and prolongs serum penicillin levels. Probenecid decreases the apparent volume of distribution and slows the rate of excretion by competitively inhibiting renal tubular secretion of penicillin. Penicillin-probenecid therapy is generally limited to those infections where very high serum levels of penicillin are necessary.

With intravenous administration, particularly in elderly patients, care should be taken because of the possibility of thrombophlebitis.

Parenteral drug products should be inspected visually for particulate matter and discoloration prior to administration whenever solution and container permit.

Do not add supplementary medication to Oxacillin Injection, USP.

Store in a freezer capable of maintaining a temperature of -20°C/-4°F or less.

DIRECTIONS FOR USE OF GALAXY PLASTIC CONTAINER

Thaw at room temperature (25°C/77°F) or under refrigeration (5°C/41°F). [DO NOT FORCE THAW BY IMMERSION IN WATER BATHS OR BY MICROWAVE IRRADIATION]. Visually inspect the container. If the outlet port protector is damaged, detached, or not present, discard container as sterility may be impaired. Components of the solution may precipitate in the frozen state and will dissolve upon reaching room temperature with little or no agitation. Potency is not affected. Mix after solution has reached room temperature. Check for minute leaks by squeezing bag firmly. If leaks are found, discard solution as sterility may be impaired. Do not use if the solution is cloudy or precipitated or if seals are not intact. The thawed solution is stable for 21 days under refrigeration or 48 hours at room temperature. Do not refreeze.

Use sterile equipment.

Caution: Do not use plastic containers in series connections. Such use could result in air embolism due to residual air being drawn from the primary container before administration of the fluid from the secondary container is complete.

Preparation for intravenous administration

1. Suspend container from eyelet support.
2. Remove protector from outlet port at bottom of container.
3. Attach administration set. Refer to complete directions accompanying set.

HOW SUPPLIED1/ STORAGE AND HANDLING

Oxacillin Injection, USP is supplied as a premixed frozen iso-osmotic solution in 50 mL single dose Galaxy plastic containers as follows:

NDC 0338-1015-41 2 grams oxacillin

Store at or below -20°C/-4°F. [See DIRECTIONS FOR USE OF GALAXY PLASTIC CONTAINER]

Handle frozen product containers with care. Product containers may be fragile in the frozen state.

Baxter and Galaxy are trademarks of Baxter International Inc. or its subsidiaries.

Baxter Healthcare Corporation
Deerfield, IL 60015 USA
Printed in USA

07-19-08-965

Rev. December 2024

PACKAGE LABEL - PRINCIPAL DISPLAY PANEL

Baxter Logo

2 g

Oxacillin Injection, USP

GALAXY
Single Dose
Container

50 mL
Iso-osmotic

NDC 0338-1015-41
Code 2G3539
Sterile Nonpyrogenic

Each 50 mL contains: Oxacillin Sodium equivalent to 2 g Oxacillin with approx.
300 mg Dextrose Hydrous, USP added to adjust osmolality and 300 mg Sodium
Citrate Hydrous, USP added as a buffer. pH adjusted with hydrochloric acid and
may have been adjusted with sodium hydroxide. pH 6.5 (6.0 to 8.5).

Dosage: Intravenously as directed by a physician. See insert.

Cautions: Do not add supplementary medication. Must not be used in series
connections. Check for minute leaks and solution clarity.

Rx only.

Do not store above -20°C/-4°F. Thaw at room temperature (25°C/77°F) or under
refrigeration (5°C/41°F). DO NOT FORCE THAW BY IMMERSION IN WATER BATHS OR BY MICROWAVE IRRADIATION. Thawed solution is stable for 21 days
under refrigeration (5°C/41°F) or 48 hours at room temperature (25°C/77°F).

Do not refreeze.

Baxter and Galaxy are registered trademarks of
Baxter International Inc.
Baxter Healthcare Corporation
Deerfield, IL 60015 USA
Made in USA

PL 2040 Plastic
07-34-63-780

Baxter Logo
Oxacillin Injection, USP
12 - 50 mL Single Dose Containers Iso-osmotic
Do not store above -20°C/-4°F. Do not refreeze.

2 g
Baxter Healthcare Corporation
Deerfield, IL 60015 USA

Thaw at room temperature (25°C/77°F) or under refrigeration (5°C/41°F). DO NOT FORCE THAW BY IMMERSION IN WATER BATHS OR BY MICROWAVE IRRADIATION. Thawed solution is stable for 21 days under refrigeration (5°C/41°F) or 48 hours at room
temperature (25°C/77°F). Do not refreeze.

Handle frozen product containers with care. Product containers may be fragile in the frozen state.

Baxter and Galaxy are registered trademarks of Baxter International Inc.

PL 2040 Plastic
07-04-65-183

NDC 0338-1015-41
Code 2G3539
*FOR BAR CODE POSITION ONLY
(01) 20303381015415

GALAXY Container
Sterile Nonpyrogenic

Each 50 mL contains: Oxacillin Sodium equivalent to 2 g Oxacillin with approx. 1.5 g of
Dextrose Hydrous, USP added to adjust osmolality and 300 mg Sodium Citrate Hydrous, USP
added as a buffer. pH adjusted with hydrochloric acid and may have been adjusted with sodium
hydroxide. pH 6.5 (6.0 to 8.5).

Dosage: Intravenously as directed by a physician. See insert.

Cautions: Do not add supplementary medication. Must not be used in series connections. Check
for minute leaks by squeezing thawed bag firmly. If leaks are found, discard bag as sterility may
be impaired. Do not use unless solution is clear. Rx only.